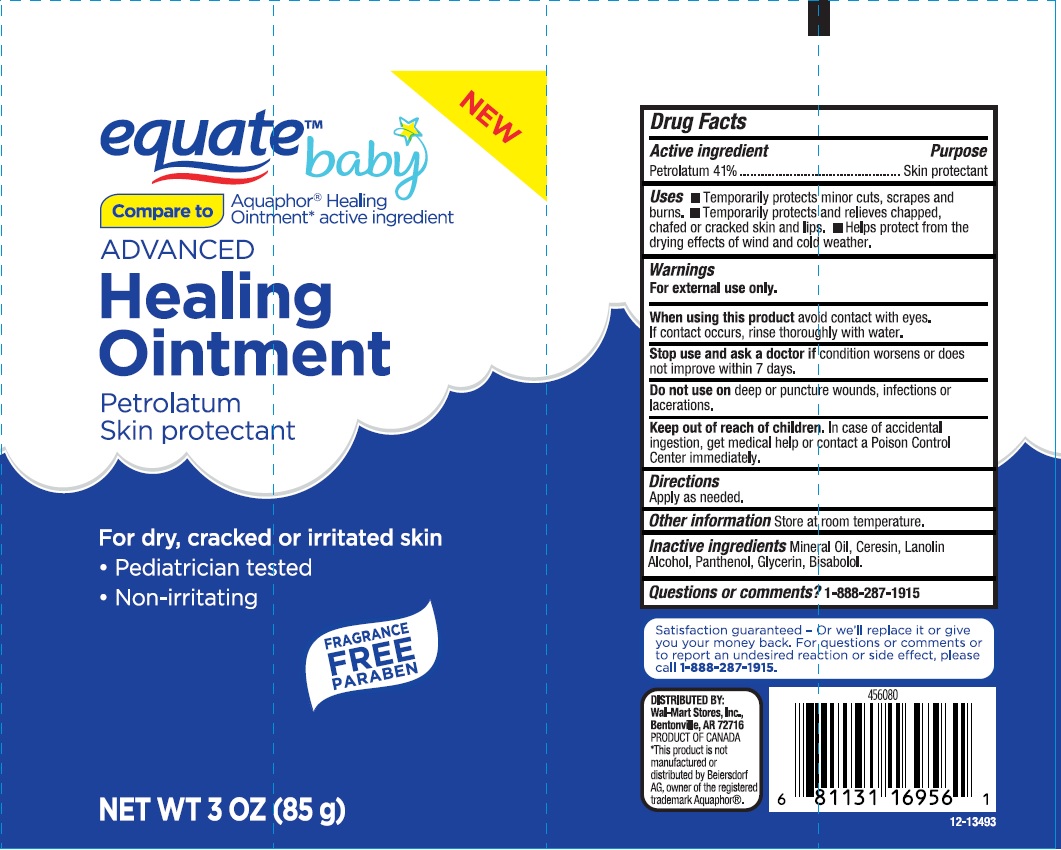 DRUG LABEL: Equate Baby Advanced Healing
NDC: 49035-055 | Form: OINTMENT
Manufacturer: Wal-Mart Store Inc
Category: otc | Type: HUMAN OTC DRUG LABEL
Date: 20170714

ACTIVE INGREDIENTS: PETROLATUM 0.41 g/1 g
INACTIVE INGREDIENTS: MINERAL OIL; CERESIN; LANOLIN ALCOHOLS; PANTHENOL; GLYCERIN; LEVOMENOL

DRUG FACTS

Active ingredient

Petrolatum 41%

Purpose

Skin protectant

Uses

- temporarily protects minor cuts, scrapes and burns
- temporarily protects and relieves chapped, chafed or cracked skin and lips
- helps protect from the drying effects of wind and cold weather

Warnings

For external use only

When using this product

avoid contact with eyes. If contact occurs, rinse thoroughly with water.

Stop use and ask a doctor if

condition worsens or does not improve within 7 days.

Do not use on

deep or puncture wounds, infections or lacerations

Keep out of reach of children.

In case of accidental ingestion, get medical help or contact a Poison Control Center immediately.

Directions

Apply as needed.

Other information

Store at room temperature.

Inactive ingredients

Mineral Oil, Ceresin, Lanolin Alcohol, Panthenol, Glycerin, Bisabolol

Questions or comments?

1-888-287-1915